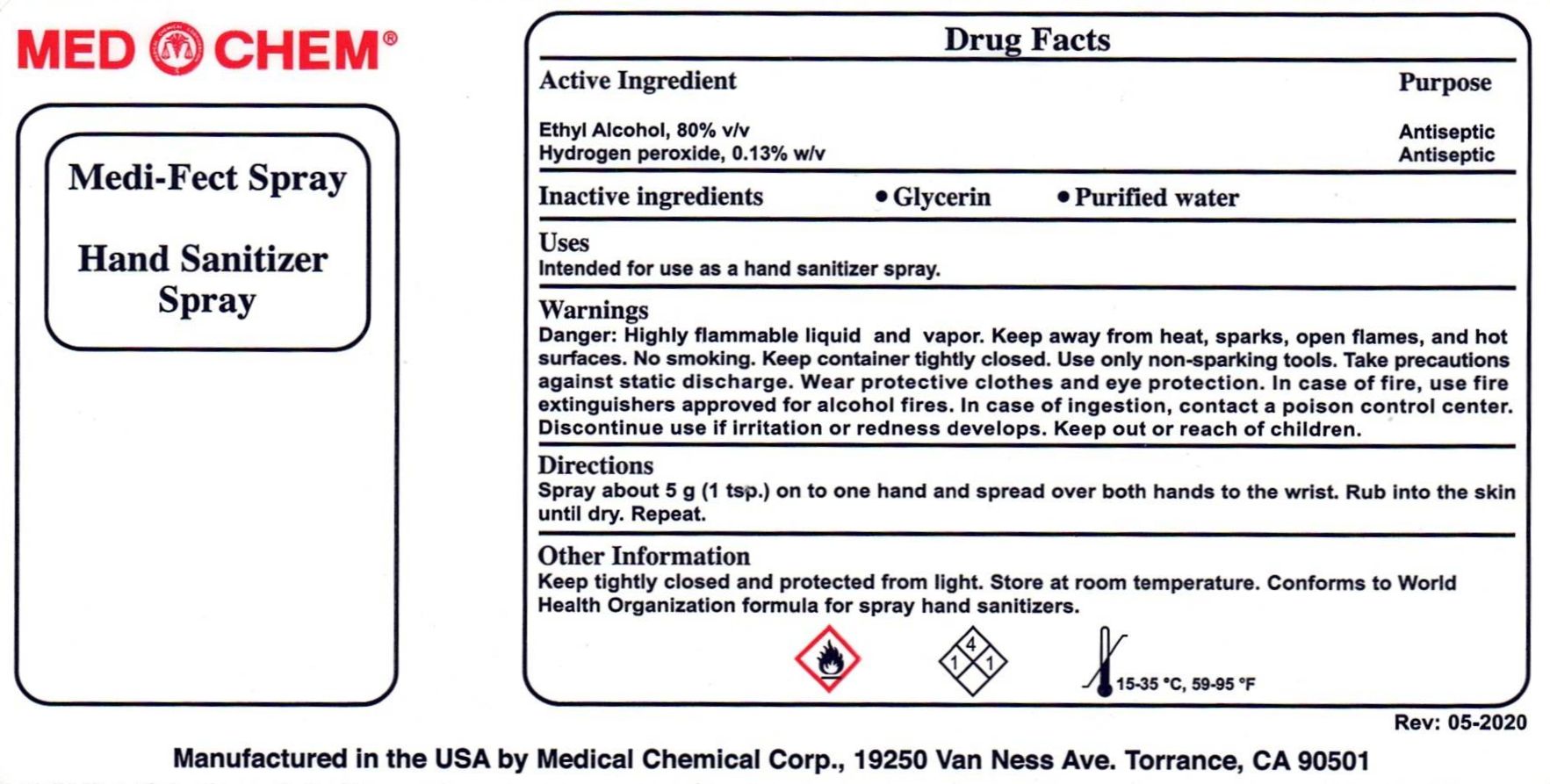 DRUG LABEL: MediFect Hand Sanitizer
NDC: 12745-901 | Form: LIQUID
Manufacturer: Medical Chemical Corporation
Category: otc | Type: HUMAN OTC DRUG LABEL
Date: 20220117

ACTIVE INGREDIENTS: HYDROGEN PEROXIDE 4.17 mL/100 mL; ALCOHOL 80 mL/100 mL
INACTIVE INGREDIENTS: GLYCERIN 1.45 mL/100 mL; WATER

MediFect Spray

This is a hand sanitizer manufactured according to the Temporary Policy for Preparation of Certain Alcohol-Based Hand Sanitizer Products During the Public Health Emergency (CoViD-19); Guidance for Industry.

The hand sanitizer is manufactured using only the following United States Pharmacopoeia (USP) grade ingredients in the preparation of the product (percentage in final product formulation) consistent with World Health Organization (WHO) recommendations:

1. Alcohol (ethanol) (USP or Food Chemical Codex (FCC) grade) (80%, volume/volume (v/v)) in an aqueous solution denatured according to Alcohol and Tobacco Tax and Trade Bureau regulations in 27 CFR part 20.
2. Glycerol (1.45% v/v).
3. Hydrogen peroxide (0.125% v/v).
4. Sterile distilled water or boiled cold water.

The firm does not add other active or inactive ingredients. Different or additional ingredients may impact the quality and potency of the product.

Active Ingredient(s)

Alcohol 80% v/v. Hydrogen peroxide, 0.13% w/v. Purpose: Antiseptic

Purpose

Antiseptic

Use

Uses: Intended for use as a hand sanitizer spray.

Warnings

Danger: Highly flammable liquid and vapor. Keep away from heat, sparks, open flames, and hot surfaces. No smoking. Keep container tightly closed. Use only non-sparking tools. Take precautions against static discharge. Wear protective clothes and eye protection. In case of fire, use fire extinguishers approved for alcohol fires. In case of ingestion, contact a poison control center. Discontinue use if irritation or redness develops. Keep out of reach of children.

Warnings

Keep out of reach of children.

Directions

Spray about 5 g (1 tsp.) on to one hand and spread over both hands to the wrist. Rub into the skin until dry. Repeat.

Other information

Keep tightly closed and protected from light. Store at room temperature. Conforms to World Health Organization formula for spary hand sanitizers.

Inactive ingredients

glycerin, purified water